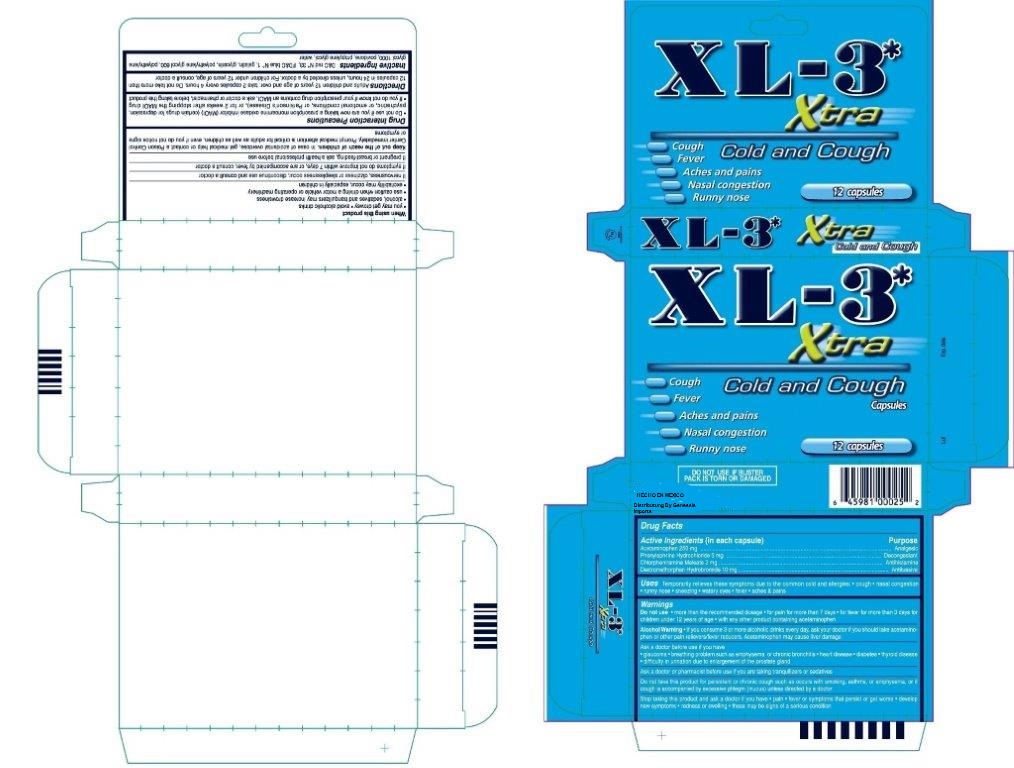 DRUG LABEL: XL3 XTRA
NDC: 69772-440 | Form: CAPSULE, LIQUID FILLED
Manufacturer: Teresa Cecena DBA Genesis
Category: otc | Type: HUMAN OTC DRUG LABEL
Date: 20150807

ACTIVE INGREDIENTS: DEXTROMETHORPHAN HYDROBROMIDE 10 mg/1 mg; PHENYLEPHRINE HYDROCHLORIDE 5 mg/1 mg; ACETAMINOPHEN 250 mg/1 mg; CHLORPHENIRAMINE MALEATE 2 mg/1 mg
INACTIVE INGREDIENTS: D&C RED NO. 33; FD&C BLUE NO. 1; GELATIN; GLYCERIN; POLYETHYLENE GLYCOL 600; POLYETHYLENE GLYCOL 1000; POVIDONE; PROPYLENE GLYCOL; WATER

DRUG FACTS

Active Ingredient in each capsule

Acetaminophen 250mg

Phenylepherine Hydrochloride 5mg

Chlorpheniramide Maleate 2mg

Dextromethorphan Hydrobromide 10mg

PURPOSE

Analgesic

Decongestant

Antihistamine

Antitussive

USES

Temporaruly relieves the symptoms due to common cold and allergies: Cough, nasal congestion, runny nose, sneezing, watery eyes, fever, aches and pains.

WARNINGS

DO NOT USE More than recommended dosage for pain more than 7 days for fever more than 3 days for children under 12 age with any other product containing acetaminophen.

WARNINGS AND PRECAUTIONS

Alcohol Warning:If you consume 3 or more alcoholic drinks every day, ask your doctor if you should take acetaminophen or other pain relivers fever reducers. Acetaminophen may casuse liver damage

Ask a doctor befor use you have

- Glaucoma, breathing problems such as emphysema or chronic bronchitis, heart disease, diabetes, thyroid disease.
- difficulty in urination due to enlagement of the prostate gland

Ask a doctor or pharmacist before use if you are taking tranquilizers or sedatives

Do not take this product for persistent or chronic cough such as occur with smoking, asthma or emphysema, or if cough is accompanied by excessive phlegm (mucis) unless directed by doctor

STOP USE

Stop taking this product and ask a doctor if yoi have pain, fever or sympoms that persist or get worse ,

new symptoms occur

redness or swelling these may be be signs of a serious condition

When using this product

- you may get drowsy avoid alcoholic drinks
- alcohol, sedatives and tranquilizers may increase drowsiness
- use caution when driving a motor vehicle or operating machinery
- excitabiloty may occur, especially in children

if nervousness, dizziness or spleeplessness occur discontinue use and consult a doctor

ASK DOCTOR

If symptoms do not improve within 7 days, or are accompanied by fever, consult a doctor

if you are pregnant or breast feeding, ask a health professional before use

KEEP OUT OF REACH OF CHILDREN

KEEP THIS AND ALL DRUGS OUT OF THE REACH OF CHILDREN. In case of accidental overdose, get medical help or contac a poison control center immediately. Prompt medical attention is critical for adults as well as children ever if you do not notice any sings or symptoms .

Drug unteraction precautions

do not use if you are taking a prescription monoamine oxidase ihibitor (MAOI) (certain drug for depression, psychoatric or emotional conditions, or parkinson's disease), or for 2 weeks after stopping the MAOI drug. If you do not know if your presctiption drug contains an MAOI, ask a doctor or pharmacist before taking this product.

DIRECTIONS

Adults and children 12 years of age and older; take 2 capsules every 4 hours. Do not take more than 12 capsules in 24 hours, unless directed by doctor. For children under 12 years of age consult a doctor

INACTIVE INGREDIENT

DC red No. 33, FDC Blue No.1, gelatin, glycerin, polyethylene glycol 600, polyethylene glycol 1000, povidone, polyethylene glycol, water.

WARNINGS

DO NOT USE More than recommended dosage for pain more than 7 days for fever more than 3 days for children under 12 age with any other product containing acetaminophen.

INDICATIONS AND USAGE

Adults and children 12 years of age and older; take 2 capsules every 4 hours. Do not take more than 12 capsules in 24 hours, unless directed by doctor. For children under 12 years of age consult a doctor